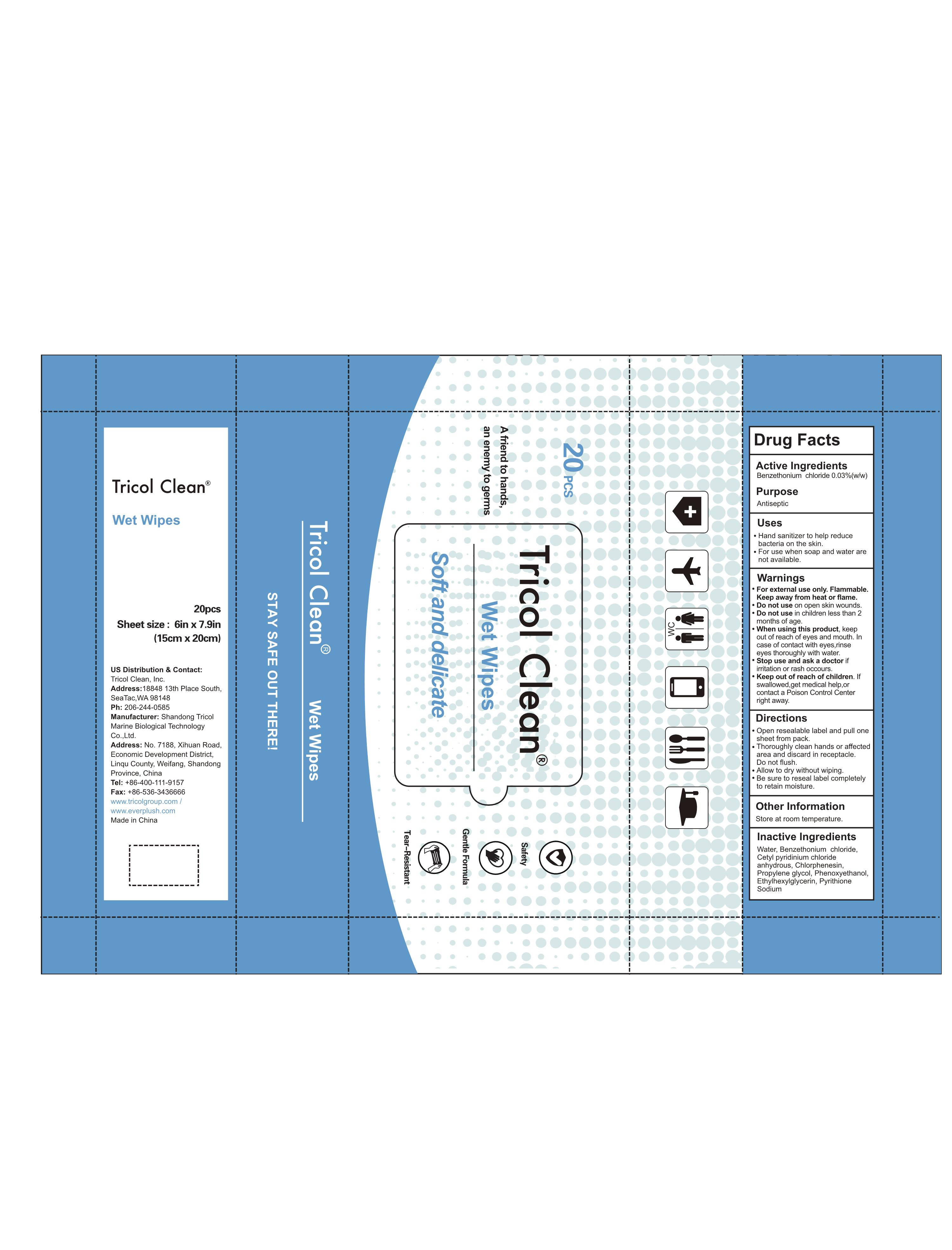 DRUG LABEL: Wet Wipes
NDC: 54156-001 | Form: CLOTH
Manufacturer: Shandong Tricol Marine Biological Technology Co.,Ltd
Category: otc | Type: HUMAN OTC DRUG LABEL
Date: 20201105

ACTIVE INGREDIENTS: BENZETHONIUM CHLORIDE 0.03 g/100 g
INACTIVE INGREDIENTS: WATER; PYRITHIONE SODIUM; CHLORPHENESIN; CETYLPYRIDINIUM CHLORIDE ANHYDROUS; PHENOXYETHANOL; PROPYLENE GLYCOL; ETHYLHEXYLGLYCERIN

Uses

1.Hand sanitizer to help reducebacteria on the skin.
2.For use when soap and water are not available.

WARNINGS

For external use only. Flammable.Keep away from heat or flame.

Do not use on open skin wounds.

Do not use in children less than 2months of age.

When using this product, keep out of reach of eyes and mouth. In case of contact with eyes,rinse eyes thoroughly with water.

Stop use and ask a doctor irritation or rash occours.

Keep out of reach of children. lf swallowed,get medical help,or contact a Poison Control Center right away.

Directions

1.open resealable label and pull one sheet from pack.
2.Thoroughly clean hands or affected area and discard in receptacle.Do not flush.
3.Allow to dry without wiping.
4.Be sure to reseal label completely to retain moisture.

Other Information

Store at room temperature.

INACTIVE INGREDIENT

Water,Benzethonium chloride,Cetylpyridinium chloride anhydrous, Chlorphenesin,Propylene glycol,Phenoxyethanol,Ethylhexylglycerin, Pyrithione Sodium

ACTIVE INGREDIENT

Benzethonium chloride

PURPOSE

Antiseptic